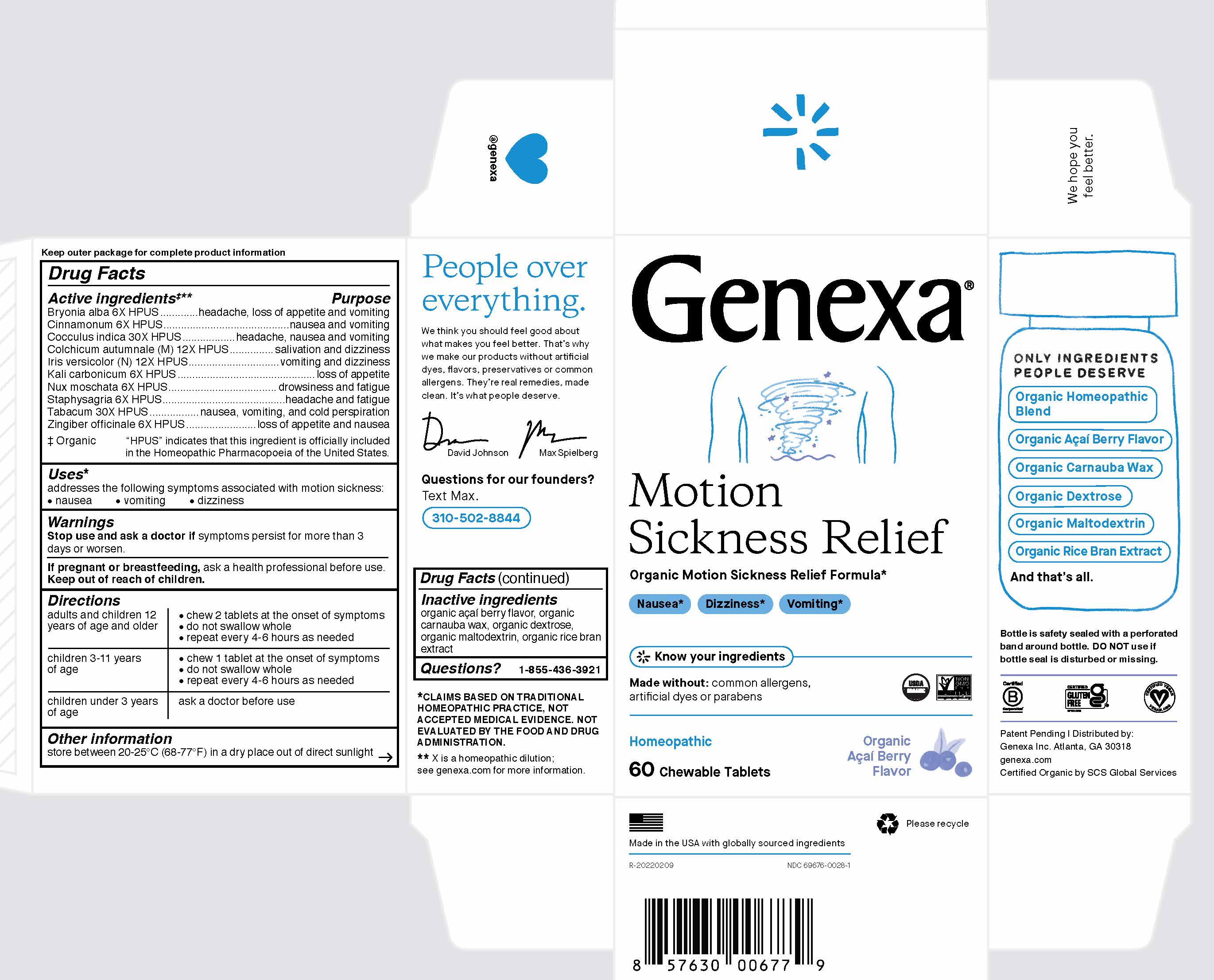 DRUG LABEL: Genexa Motion Sickness Relief
NDC: 69676-0028 | Form: TABLET, CHEWABLE
Manufacturer: Genexa Inc.
Category: homeopathic | Type: HUMAN OTC DRUG LABEL
Date: 20230120

ACTIVE INGREDIENTS: BRYONIA ALBA WHOLE 6 [hp_X]/1 1; CINNAMON 6 [hp_X]/1 1; ANAMIRTA COCCULUS SEED 30 [hp_X]/1 1; COLCHICUM AUTUMNALE BULB 12 [hp_X]/1 1; IRIS VERSICOLOR ROOT 12 [hp_X]/1 1; POTASSIUM CARBONATE 6 [hp_X]/1 1; NUTMEG 6 [hp_X]/1 1; DELPHINIUM STAPHISAGRIA SEED 6 [hp_X]/1 1; TOBACCO LEAF 30 [hp_X]/1 1; GINGER 6 [hp_X]/1 1
INACTIVE INGREDIENTS: MALTODEXTRIN; RICE BRAN; DEXTROSE; CARNAUBA WAX

Motion Sickness Relief

Keep outer package for complete product information
Drug Facts

Active ingredients‡**

Bryonia alba 6X HPUS

Cinnamonum 6X HPUS

Cocculus indica 30X HPUS

Colchicum autumnale (M) 12X

Iris versicolor (N) 12X HPUS

Kali carbonicum 6X HPUS

Nux moschata 6X HPUS

Staphysagria 6X HPUS

Tabacum 30X HPUS

Zingiber officinale 6X HPUS

‡ Organic

"HPUS" indicates that this ingredient is officially included in the Homeopathic Pharmacopoeia of the United States.

Purpose

headache, loss of appetite and vomiting

nausea and vomiting

headache, nausea and vomiting

salivation and dizziness

vomiting and dizziness

loss of appetite

drowsiness and fatigue

headache and fatigue

nausea, vomiting and cold perspiration

loss of appetite and nausea

Uses*

addresses the following symptoms associated with motion sickness:

- nausea
- vomiting
- dizziness

Warnings

Stop use and ask a doctor if symptoms persist for more than 3 days or worsen.

PREGNANCY OR BREAST FEEDING

If pregnant or breastfeeding, ask a health professional before use.

Keep out of reach of children.

Directions

adults and children 12 years; of age and older | - chew 2 tablets at the onset of symptoms - do not swallow whole - repeat every 4-6 hours as needed
children 3-11 years of age | - chew 1 tablet at the onset of symptoms - do not swallow whole - repeat every 4-6 hours as needed
children under 3 years of age | ask a doctor before use

Other information

store between 20-25° C (68-77° F) in a dry place out of direct sunlight.

Inactive ingredients

organic acai berry flavor, organic carnauba wax, organic dextrose, organic maltodextrin, organic rice bran extract

Questions?

1-855-436-3921

* CLAIMS BASED ON TRADITIONAL HOMEOPATHIC PRACTICE, NOT ACCEPTED MEDICAL EVIDENCE. NOT EVALUATED BY THE FOOD AND DRUG ADMINISTRATION.

** X is a homeopathic dilution:

see genexa.com for more information.

Bottle is safety sealed with a perforated band around the bottle. DO NOT use if bottle seal is disturbed or missing.

Patent Pending | Distributed by:

Genexa Inc. Atlanta, GA 30318

genexa.com
Certified Organic by SCS Global Services

Made in the USA with globally sourced ingredients

R-20220209

NDC 69676-0028-1

PACKAGE LABEL

Genexa

Motion Sickness Relief

Organic Motion Sickness Relief Formula*Nausea*

Nausea*

Dizziness*

Vomiting*

Know you ingredients

Made with Organic Acai Berry Flavor

Made without: common allergens, artificial dyes, or parabens

Homeopathic

60 Chewable Tablets